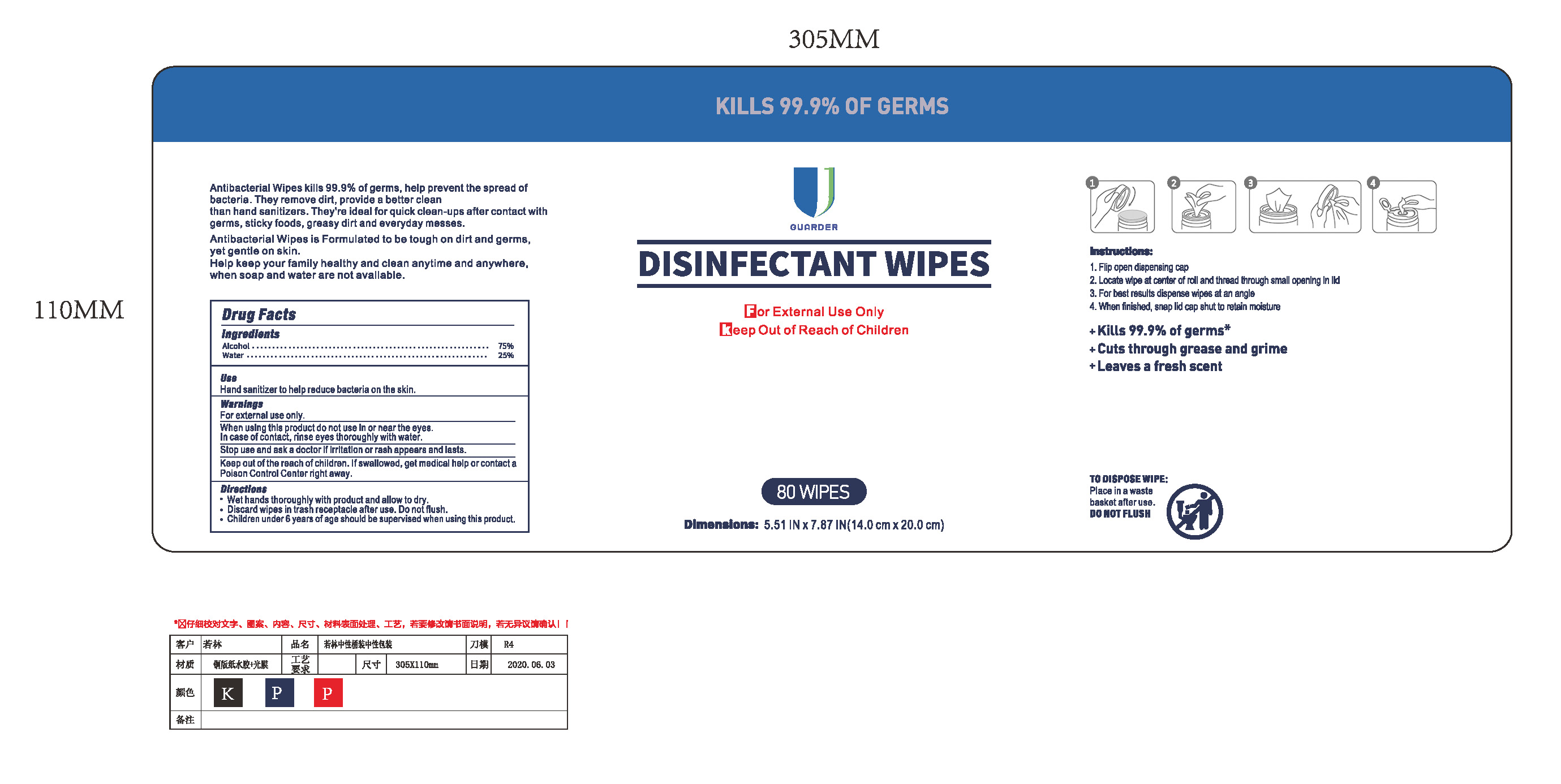 DRUG LABEL: Antibacterial wipes (75% Alcohol)
NDC: 79795-001 | Form: CLOTH
Manufacturer: NanTong Guarder Medical Technology Co.,Ltd.
Category: otc | Type: HUMAN OTC DRUG LABEL
Date: 20200727

ACTIVE INGREDIENTS: ALCOHOL 0.75 g/1 1
INACTIVE INGREDIENTS: WATER

Antibacterial wipes (75% Alcohol)

Active Ingredient(s)

Alcohol 75% v/v. Purpose: Antiseptic

Purpose

Antiseptic

Use

Hand Sanitizer to help reduce bacteria on the skin.

Warnings

For external use only. Flammable.

When using this product keep out of eyes, ears, and mouth. In case of contact with eyes, rinse eyes thoroughly with water.

Stop use and ask a doctor if irritation or rash appears and lasts.

Keep out of the reach of children. If swallowed, get medcial help or contact a poison control center right away.

Do not use

- in children less than 2 months of age
- on open skin wounds

When using this product keep out of eyes, ears, and mouth. In case of contact with eyes, rinse eyes thoroughly with water.
Stop use and ask a doctor if irritation or rash occurs. These may be signs of a serious condition.
Keep out of reach of children. If swallowed, get medical help or contact a Poison Control Center right away.

Stop use and ask a doctor if irritation or rash occurs. These may be signs of a serious condition.

Keep out of reach of children. If swallowed, get medical help or contact a Poison Control Center right away.

Directions

Wet hands thoroughly with product and allow to dry.

Dicard wipes in trash receptacle after use. Do not flush.

Children under 6 years of age should be supervised when using this product.

Other information

- Store between 15-30C (59-86F)
- Avoid freezing and excessive heat above 40C (104F)

Inactive ingredients

Water

Package Label - Principal Display Panel

80wipes in onebox NDC: 79795-001-09